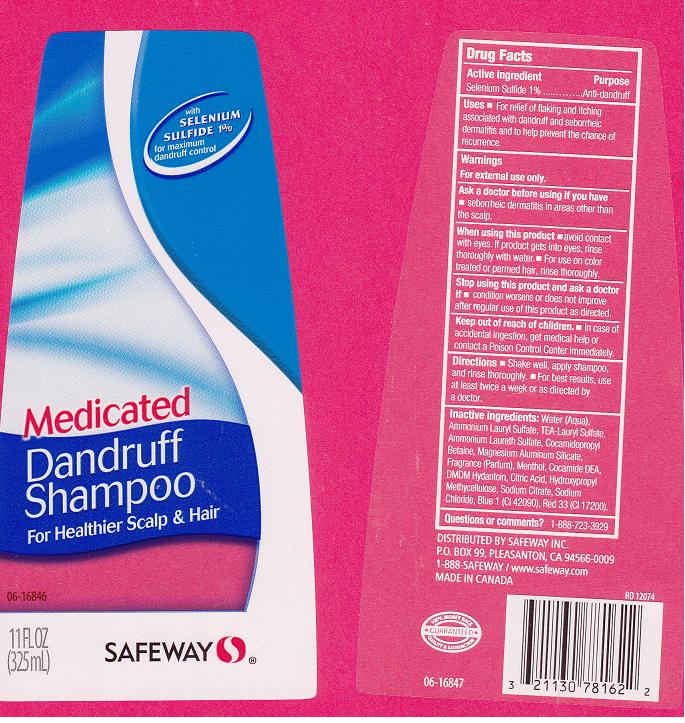 DRUG LABEL: SAFEWAY
NDC: 21130-617 | Form: SHAMPOO
Manufacturer: SAFEWAY INC.
Category: otc | Type: HUMAN OTC DRUG LABEL
Date: 20120605

ACTIVE INGREDIENTS: SELENIUM SULFIDE 1 mL/100 mL
INACTIVE INGREDIENTS: WATER; AMMONIUM LAURYL SULFATE; TROLAMINE LAURYL SULFATE; AMMONIUM LAURETH-2 SULFATE; COCAMIDOPROPYL BETAINE; MAGNESIUM ALUMINUM SILICATE; MENTHOL; COCO DIETHANOLAMIDE; DMDM HYDANTOIN; CITRIC ACID MONOHYDRATE; HYPROMELLOSE 2208 (100 MPA.S); SODIUM CITRATE; SODIUM CHLORIDE; D&C BLUE NO. 4; D&C RED NO. 33

DRUG FACTS

ACTIVE INGREDIENT

SELENIUM SULFIDE 1%

PURPOSE

ANTI-DANDRUFF

USES

FOR RELIEF OF FLAKING AND ITCHING ASSOCIATED WITH DANDRUFF AND SEBORRHEIC DERMATITIS AND TO HELP PREVENT THE CHANCE OF RECURRENCE.

WARNINGS

FOR EXTERNAL USE ONLY.

ASK A DOCTOR BEFORE USING IF YOU HAVE

SEBORRHEIC DERMATITIS IN AREAS OTHER THAN THE SCALP.

WHEN USING THIS PRODUCT

AVOID CONTACT WITH EYES. IF PRODUCT GETS INTO EYES, RINSE THOROUGHLY WITH WATER. FOR USE ON COLOR TREATED OR PERMED HAIR, RINSE THOROUGHLY.

STOP USING THIS PRODUCT AND ASK A DOCTOR IF

CONDITION WORSENS O DOES NOT IMPROVE AFTER REGULAR USE OF THIS PRODUCT AS DIRECTED.

KEEP OUT OF REACH OF CHILDREN

IN CASE OF ACCIDENTAL INGESTION, GET MEDICAL HELP OR CONTACT A POISON CONTROL CENTER IMMEDIATELY.

DIRECTIONS

SHAKE WELL, APPLY SHAMPOO, AND RINSE THOROUGHLY. FOR BEST RESULTS, USE AT LEAST TWICE A WEEK OR AS DIRECTED BY A DOCTOR.

INACTIVE INGREDIENTS

WATER (AQUA), AMMONIUM LAURYL SULFATE, TEA-LAURYL SULFATE, AMMONIUM LAURETH SULFATE, COCAMIDOPROPYL BETAINE, MAGNESIUM ALUMINUM SILICATE, FRAGRANCE (PARFUM), MENTHOL, COCAMIDE DEA, DMDM HYDANTOIN, CITRIC ACID, HYDROXYPROPYL METHYLCELLULOSE, SODIUM CITRATE, SODIUM CHLORIDE, BLUE 1 (CI 42090), RED 33 (CI 17200).

QUESTIONS OR COMMENTS?

1-888-723-3929